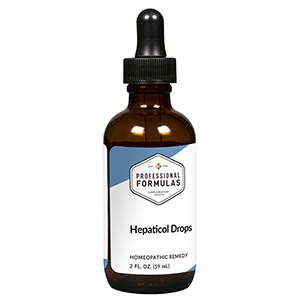 DRUG LABEL: Hepaticol Drops
NDC: 63083-5008 | Form: LIQUID
Manufacturer: Professional Complementary Health Formulas
Category: homeopathic | Type: HUMAN OTC DRUG LABEL
Date: 20190815

ACTIVE INGREDIENTS: MILK THISTLE 2 [hp_X]/59 mL; GINGER 2 [hp_X]/59 mL; VERONICASTRUM VIRGINICUM WHOLE 3 [hp_X]/59 mL; BERBERIS VULGARIS ROOT BARK 4 [hp_X]/59 mL; CHELIDONIUM MAJUS WHOLE 4 [hp_X]/59 mL; CYSTEINE 4 [hp_X]/59 mL; MAGNESIUM CHLORIDE 4 [hp_X]/59 mL; SODIUM CHLORIDE 5 [hp_X]/59 mL; ATROPINE SULFATE 6 [hp_X]/59 mL; BRYONIA ALBA ROOT 6 [hp_X]/59 mL; BEEF LIVER 6 [hp_X]/59 mL; SODIUM SULFATE 6 [hp_X]/59 mL; UBIDECARENONE 12 [hp_X]/59 mL; LYCOPODIUM CLAVATUM SPORE 12 [hp_X]/59 mL
INACTIVE INGREDIENTS: ALCOHOL; WATER

HHD

ACTIVE INGREDIENTS

Carduus marianus 2X
Zingiber officinale 2X
Leptandra virginica 3X
Berberis vulgaris 4X
Chelidonium majus 4X
L-Cysteine 4X
Magnesia muriatica 4X
Natrum muriaticum 5X
Atropinum sulphuricum 6X
Bryonia 6X
Liver 6X
Natrum sulphuricum 6X
Coenzyme Q10 12X
Lycopodium clavatum 12X

QUESTIONS

Professional Formulas

PO Box 2034 Lake Oswego, OR 97035

INDICATIONS

For the temporary relief of minor abdominal pain or swelling, fatigue, irritability, nausea or vomiting, constipation, loss of appetite, or itchy skin.*

PURPOSE

*Claims based on traditional homeopathic practice, not accepted medical evidence. Not FDA evaluated.

WARNINGS

Severe or persistent symptoms may be serious. Consult a doctor promptly. Keep out of the reach of children. In case of overdose, get medical help or contact a poison control center right away. If pregnant or breastfeeding, ask a healthcare professional before use.

Keep out of the reach of children.

PREGNANCY OR BREAST FEEDING

If pregnant or breastfeeding, ask a healthcare professional before use.

DIRECTIONS

Place drops under tongue 30 minutes before/after meals. Adults and children 12 years and over: Take 10 drops up to 3 times per day. Consult a physician for use in children under 12 years of age.

OTHER INFORMATION

Tamper resistant. If seal is broken, do not use. After opening, close container tightly and store at room temperature away from heat.

INACTIVE INGREDIENTS

20% ethanol, purified water.

LABEL

Est 1985

Professional Formulas

Complementary Health

Hepaticol Drops

Homeopathic Remedy

2 FL. OZ. (59 mL)